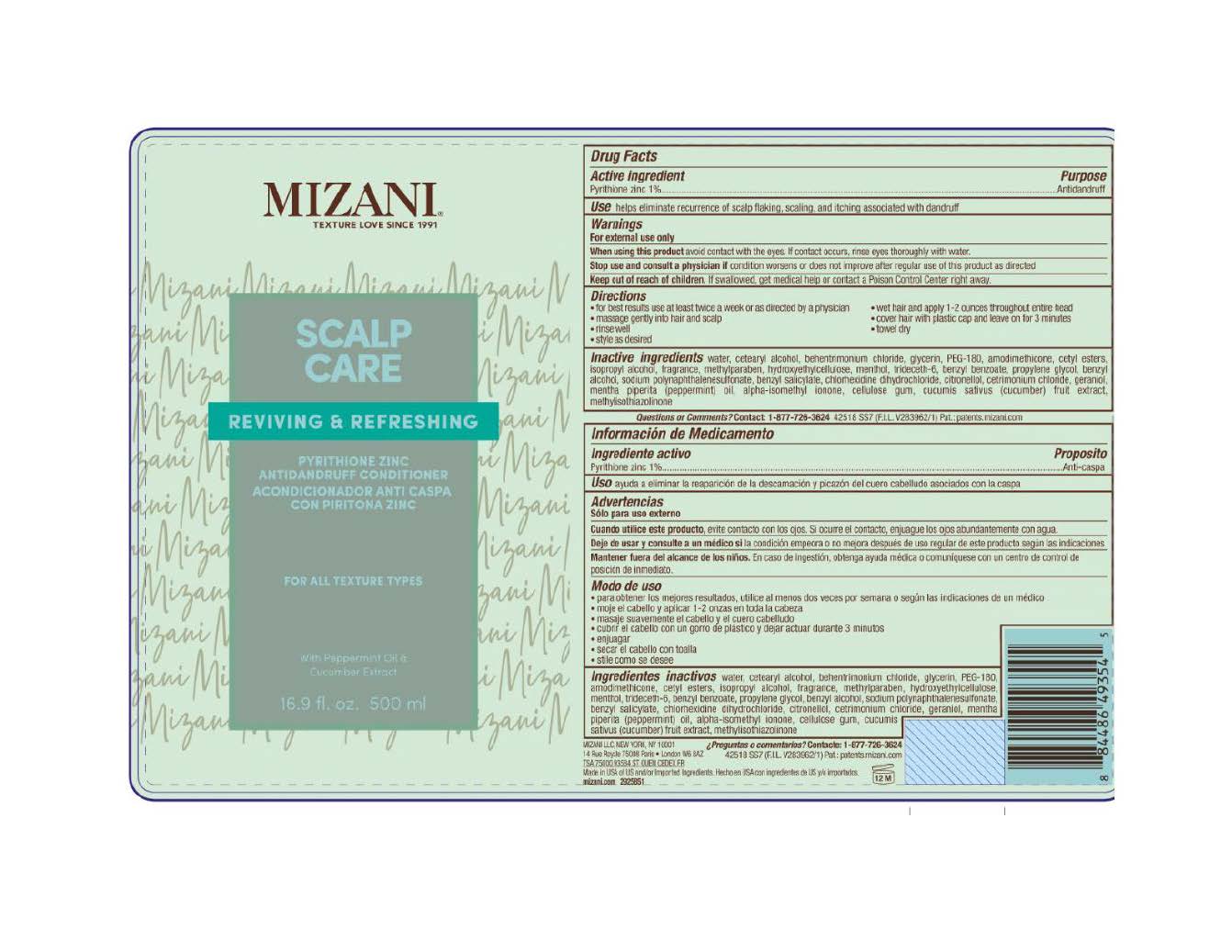 DRUG LABEL: Mizani Scalp Care Conditioner Antidandruff Conditioner
NDC: 49967-389 | Form: LOTION
Manufacturer: L'Oreal USA Products Inc
Category: otc | Type: HUMAN OTC DRUG LABEL
Date: 20231211

ACTIVE INGREDIENTS: PYRITHIONE ZINC 10 mg/1 mL
INACTIVE INGREDIENTS: WATER; CETOSTEARYL ALCOHOL; BEHENTRIMONIUM CHLORIDE; POLYETHYLENE GLYCOL 8000; AMODIMETHICONE (1300 CST); CETYL ESTERS WAX; ISOPROPYL ALCOHOL; METHYLPARABEN; HYDROXYETHYL CELLULOSE, UNSPECIFIED; MENTHOL; TRIDECETH-6; BENZYL BENZOATE; PROPYLENE GLYCOL; BENZYL ALCOHOL; BENZYL SALICYLATE; CHLORHEXIDINE HYDROCHLORIDE; .BETA.-CITRONELLOL, (R)-; CETRIMONIUM CHLORIDE; GERANIOL; PEPPERMINT OIL; ISOMETHYL-.ALPHA.-IONONE; CARBOXYMETHYLCELLULOSE SODIUM, UNSPECIFIED; CUCUMBER; METHYLISOTHIAZOLINONE

Drug Facts

Active ingredient

Pyrithione zinc 1%

Purpose

Antidandruff

Use

helps eliminate recurrence of scalp flaking, scaling, and itching associated with dandruff

Warnings

For external use only

When using this product

do not get into eyes. If contact occurs, rinse eyes thoroughly with water.

Stop use and consult a physician if

condition worsens or does not improve after regular use

Keep out of reach of children.

If swallowed, get medical help or contact a Poison Control Center right away.

Directions

- for best results use at least twice a week or as directed by a physician
- wet hair and apply 1 - 2 ounces throughout entire head
- massage gently into hair and scalp
- cover hair with plastic cap and leave on for 3 minutes
- rinse well
- towel dry
- style as desired

Inactive ingredients

water, cetearyl alcohol, behentrimonium chloride, glycerin, PEG-180, amodimethicone, cetyl esters, isopropyl alcohol, fragrance, methylparaben, hydroxyethylcellulose, menthol, trideceth-6, benzyl benzoate, propylene glycol, benzyl alcohol, sodium polynaphthalenesulfonate, benzyl salicylate, chlorhexidine dihydrochloride, citronellol, cetrimonium chloride, geraniol, mentha piperita (peppermint) oil, alpha-isomethyl ionone, cellulose gum, cucumis sativus (cucumber) fruit extract, methylisothiazolinone